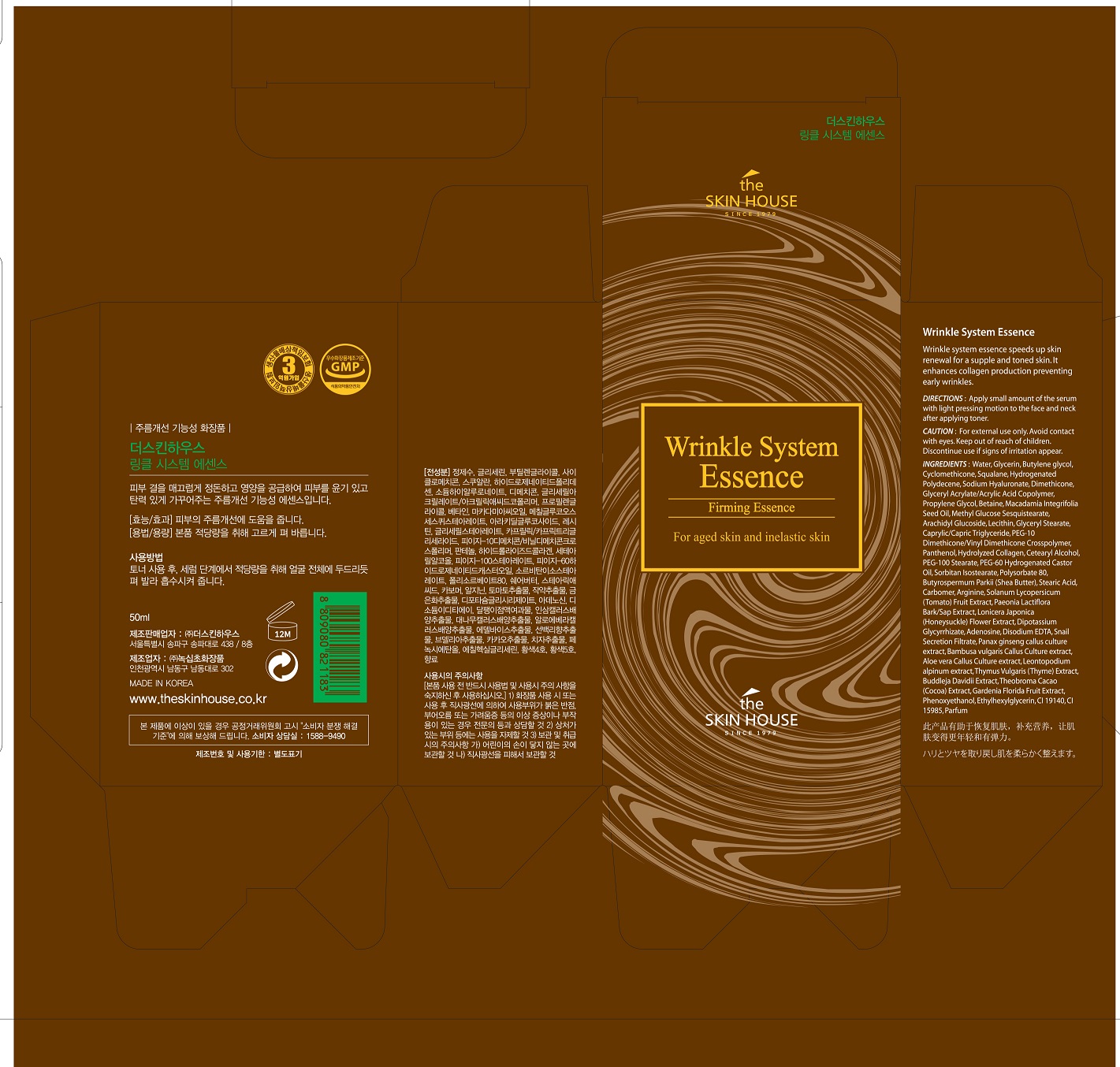 DRUG LABEL: THE SKIN HOUSE Wrinkle System Essence
NDC: 73590-0034 | Form: LIQUID
Manufacturer: NOKSIBCHO cosmetic Co., Ltd.
Category: otc | Type: HUMAN OTC DRUG LABEL
Date: 20200331

ACTIVE INGREDIENTS: ADENOSINE 0.04 g/100 mL
INACTIVE INGREDIENTS: WATER

Drug Facts

ACTIVE INGREDIENT

adenosine

INACTIVE INGREDIENT

Water
Glycerin
Butylene glycol
Cyclomethicone
Squalane
Hydrogenated Polydecene
Sodium Hyaluronate
Dimethicone
Glyceryl Acrylate/Acrylic Acid Copolymer
Propylene Glycol
Betaine
Macadamia Integrifolia Seed Oil
Methyl Glucose Sesquistearate
Arachidyl Glucoside
Lecithin
Caprylic/Capric Triglyceride
PEG-10 Dimethicone/Vinyl Dimethicone Crosspolymer
Panthenol
Hydrolyzed Collagen
Cetearyl Alcohol
PEG-100 Stearate
Glyceryl Stearate
PEG-60 Hydrogenated Castor Oil
Sorbitan Isostearate
Polysorbate 80
Butyrospermum Parkii (Shea Butter)
Stearic Acid
Carbomer
Arginine
Solanum Lycopersicum (Tomato) Fruit Extract
Paeonia Lactiflora Bark/Sap Extract
Lonicera Japonica (Honeysuckle) Flower Extract
Dipotassium Glycyrrhizate
Disodium EDTA
Snail Secretion Filtrate
Panax ginseng callus culture extract
Bambusa vulgaris Callus Culture extract
Aloe vera Callus Culture extract
Leontopodium alpinum extract
Thymus Vulgaris (Thyme) Extract
Buddleja Davidii Extract
Theobroma Cacao (Cocoa) Extract
Gardenia Florida Fruit Extract
Phenoxyethanol
Ethylhexylglycerin
CI 19140
CI 15985
Parfum

PURPOSE

wrinkle care

keep out of reach of the children

INDICATIONS AND USAGE

apply proper amount to the skin

WARNINGS

For external use only
When using this product

■ if the following symptoms occurs after use, stop use and consult with a skin specialist

red specks, swelling, itching

■ don’t use on the part where there is injury, eczema, or dermatitis

Keep out of reach of children

■ if swallowed, get medical help or contact a person control center immediately